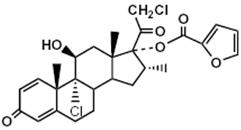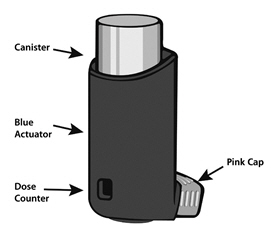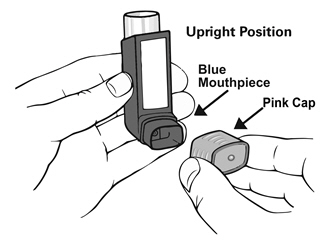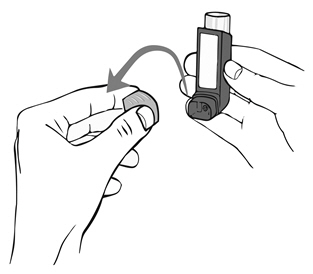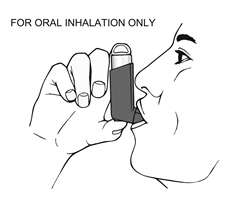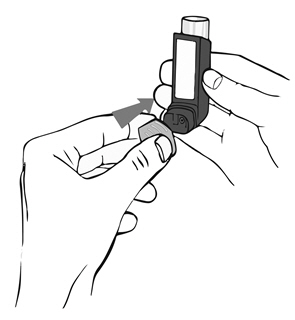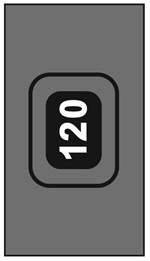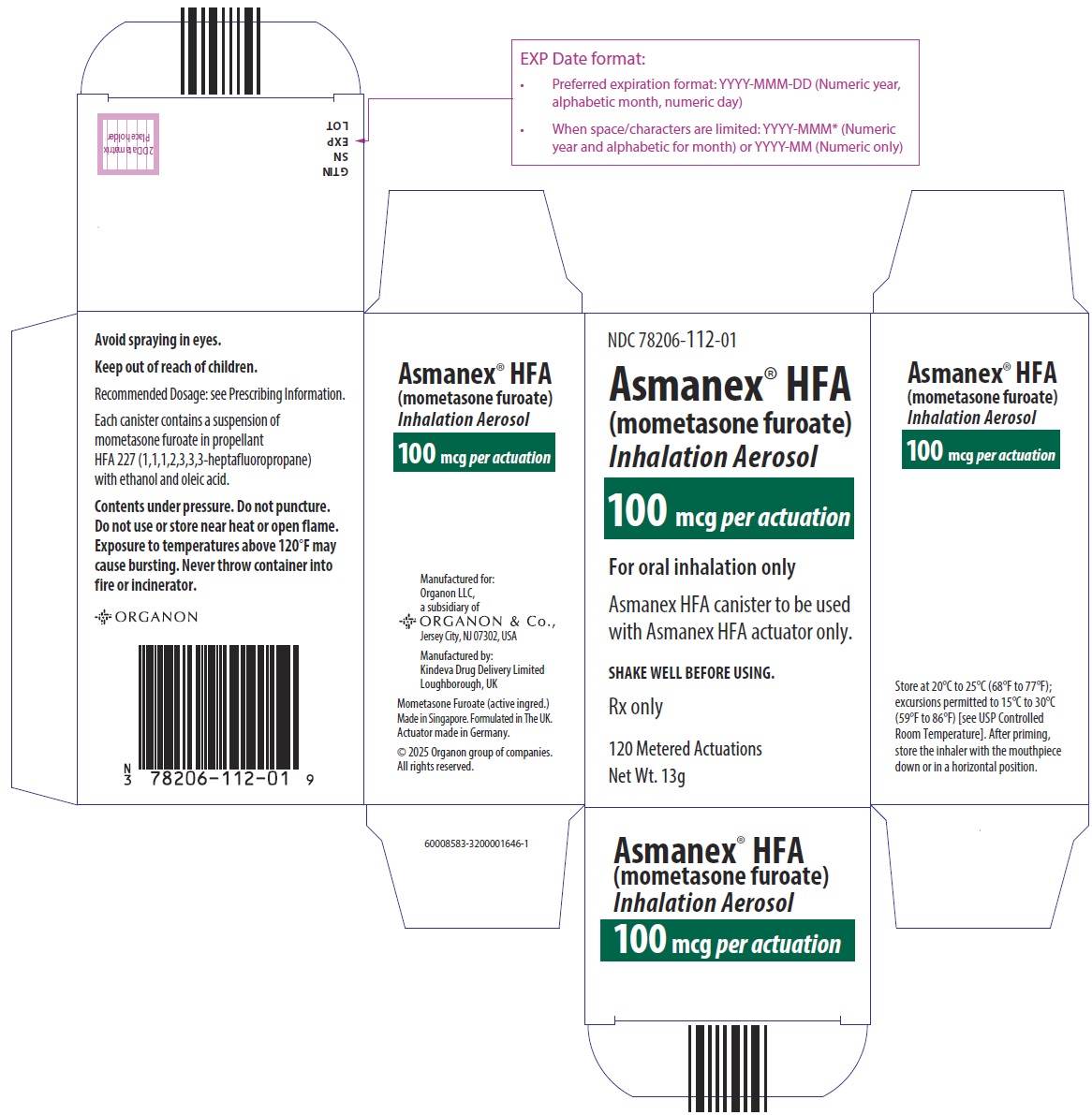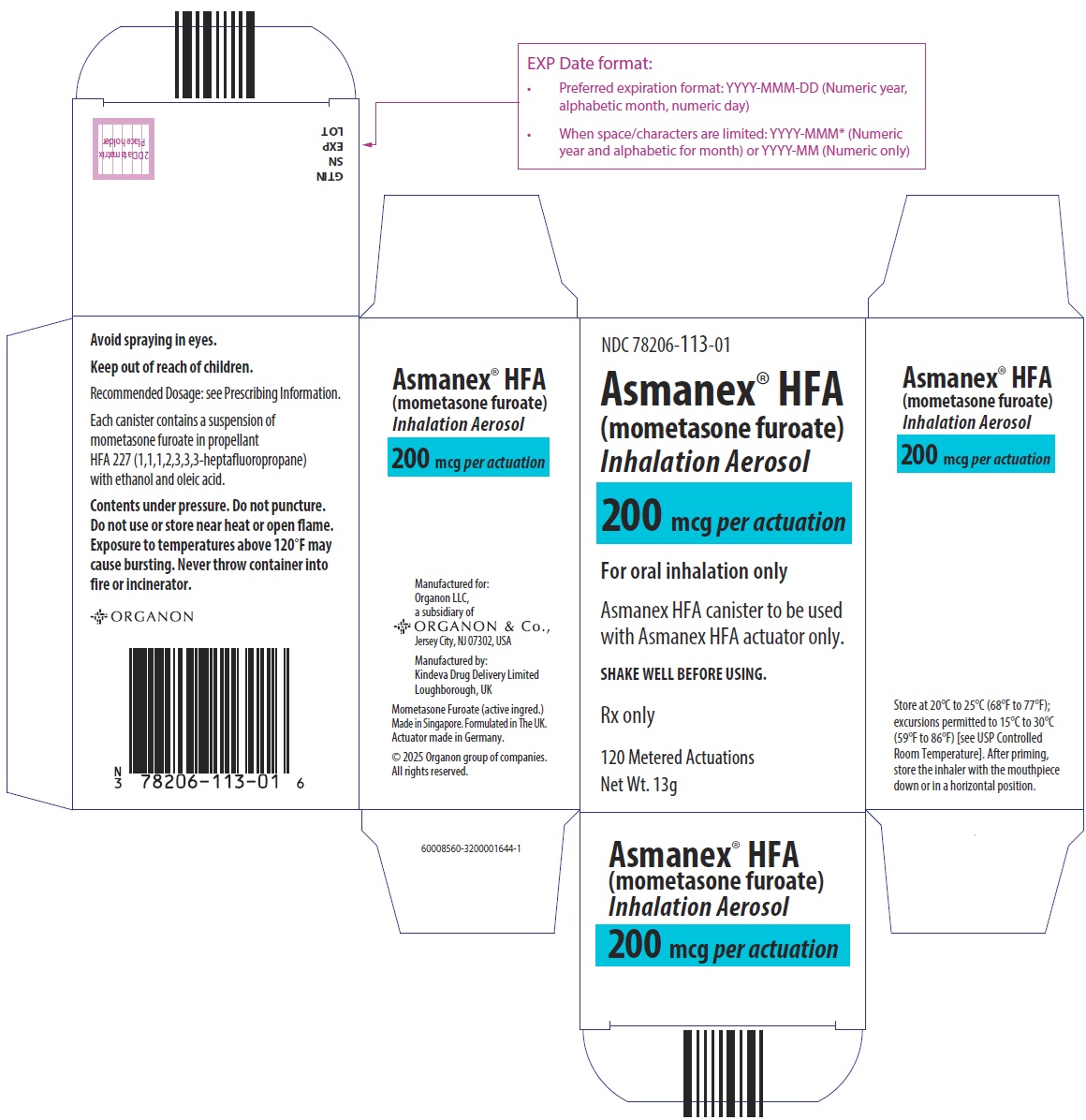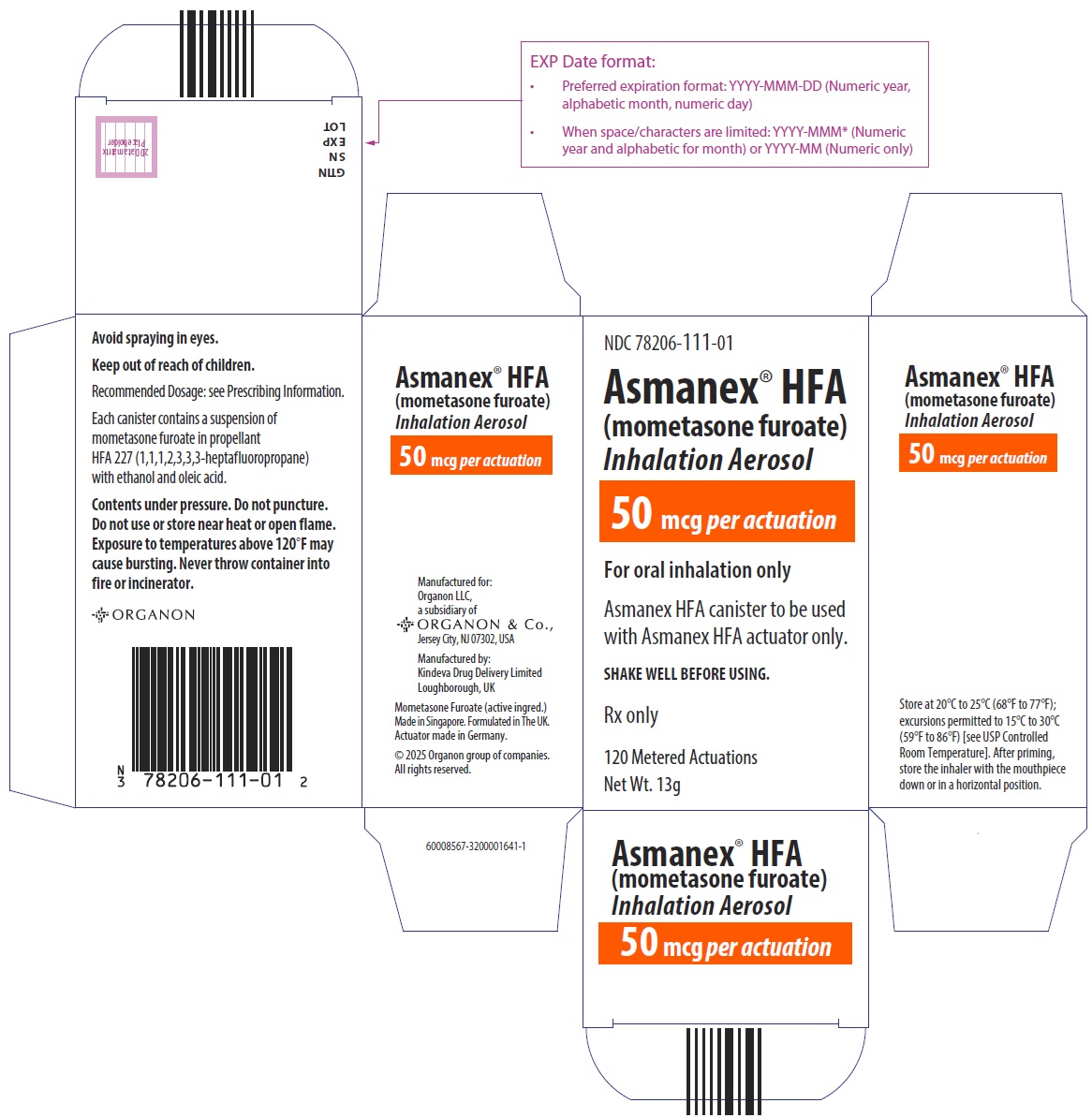 DRUG LABEL: ASMANEX HFA
NDC: 78206-112 | Form: AEROSOL
Manufacturer: Organon LLC
Category: prescription | Type: HUMAN PRESCRIPTION DRUG LABEL
Date: 20260122

ACTIVE INGREDIENTS: MOMETASONE FUROATE 100 ug/1 1
INACTIVE INGREDIENTS: ALCOHOL; OLEIC ACID; APAFLURANE

HIGHLIGHTS OF PRESCRIBING INFORMATION

These highlights do not include all the information needed to use ASMANEX HFA safely and effectively. See full prescribing information for ASMANEX HFA.
ASMANEX® HFA (mometasone furoate) inhalation aerosol, for
oral inhalation use
Initial U.S. Approval: 1987

1 INDICATIONS AND USAGE

ASMANEX HFA is a corticosteroid indicated for:

- Maintenance treatment of asthma as prophylactic therapy in patients 5 years of age and older. (1.1)

Important limitations:

- Not indicated for the relief of acute bronchospasm. (1.1)

2 DOSAGE AND ADMINISTRATION

For oral inhalation only. (2.1)

- Treatment of asthma in patients 12 years of age and older: 2 inhalations twice daily of ASMANEX HFA 100 mcg or 200 mcg. Starting dosage is based on prior asthma therapy. (2.2)
- Treatment of asthma in patients aged 5 to less than 12 years: 2 inhalations twice daily of ASMANEX HFA 50 mcg. (2.2)

3 DOSAGE FORMS AND STRENGTHS

- Inhalation aerosol containing 50 mcg, 100 mcg, or 200 mcg of mometasone furoate per actuation. (3)

4 CONTRAINDICATIONS

- Primary treatment of status asthmaticus or acute episodes of asthma requiring intensive measures. (4.1)
- Hypersensitivity to any of the ingredients of ASMANEX HFA. (4.2)

5 WARNINGS AND PRECAUTIONS

- Deterioration of asthma and acute episodes: ASMANEX HFA should not be used for relief of acute symptoms. Patients require immediate re-evaluation during rapidly deteriorating asthma. (5.1)
- Localized infections: Candida albicans infection of the mouth and throat may occur. Monitor patients periodically for signs of adverse effects on the oral cavity. After dosing, advise patients to rinse their mouth with water and spit out contents without swallowing. (5.2)
- Immunosuppression: Potential worsening of existing tuberculosis, fungal, bacterial, viral, or parasitic infection; or ocular herpes simplex infections. More serious or even fatal course of chickenpox or measles can occur in susceptible patients. Use with caution in patients with these infections because of the potential for worsening of these infections. (5.3)
- Transferring patients from systemic corticosteroids: Risk of impaired adrenal function when transferring from oral steroids. Wean patients slowly from systemic corticosteroids if transferring to ASMANEX HFA. (5.4)
- Hypercorticism and adrenal suppression: May occur with very high dosages or at the regular dosage in susceptible individuals. If such changes occur, discontinue ASMANEX HFA slowly. (5.5)
- Strong cytochrome P450 3A4 inhibitors (e.g., ritonavir): Risk of increased systemic corticosteroid effects. Exercise caution when used with ASMANEX HFA. (5.6)
- Paradoxical bronchospasm: Discontinue ASMANEX HFA and institute alternative therapy if paradoxical bronchospasm occurs. (5.7)
- Hypersensitivity reactions including anaphylaxis: Hypersensitivity reactions, such as urticaria, flushing, allergic dermatitis, bronchospasm, rash, pruritus, angioedema, and anaphylactic reaction may occur. Discontinue ASMANEX HFA if such reactions occur. (5.8)
- Decreases in bone mineral density: Monitor patients with major risk factors for decreased bone mineral content. (5.9)
- Effects on growth: Monitor growth of pediatric patients. (5.10)
- Glaucoma and cataracts: Consider referral to an ophthalmologist in patients who develop ocular symptoms or use ASMANEX HFA long term. (5.11)

6 ADVERSE REACTIONS

Most common adverse reactions (reported in greater than or equal to 3% of patients) included:

- nasopharyngitis, headache, sinusitis, bronchitis, and influenza. (6.1)

To report SUSPECTED ADVERSE REACTIONS, contact Organon LLC, a subsidiary of Organon & Co., at 1-844-674-3200 or FDA at 1-800-FDA-1088 or www.fda.gov/medwatch.

7 DRUG INTERACTIONS

- Strong cytochrome P450 3A4 inhibitors (e.g., ritonavir): Use with caution. May cause increased systemic corticosteroid effects. (7.1)

8 USE IN SPECIFIC POPULATIONS

- Hepatic impairment: Monitor patients for signs of increased drug exposure. (8.6)

FULL PRESCRIBING INFORMATION

1 INDICATIONS AND USAGE

1.1 Treatment of Asthma

ASMANEX® HFA is indicated for the maintenance treatment of asthma as prophylactic therapy in patients 5 years of age and older.

Important Limitations of Use

- ASMANEX HFA is NOT indicated for the relief of acute bronchospasm.

2 DOSAGE AND ADMINISTRATION

2.1 Administration Information

Administer ASMANEX HFA only by the orally inhaled route [see Instructions for Use in the Patient Information leaflet]. After each dose, advise patients to rinse their mouth with water and, without swallowing, spit out the contents to help reduce the risk of oropharyngeal candidiasis.

Remove the cap from the mouthpiece of the actuator before using ASMANEX HFA.

Prime ASMANEX HFA before using for the first time by releasing 4 test sprays into the air, away from the face, shaking well before each spray. In cases where the inhaler has not been used for more than 5 days, prime the inhaler again by releasing 4 test sprays into the air, away from the face, shaking well before each spray.

Only use the ASMANEX HFA canister with the ASMANEX HFA actuator. Do not use the ASMANEX HFA actuator with any other inhalation drug product. Do not use actuators from other products with the ASMANEX HFA canister.

2.2 Recommended Dosage

Administer ASMANEX HFA as two inhalations twice daily every day (morning and evening) by the orally inhaled route. Shake well prior to each inhalation. If symptoms arise between doses, use an inhaled short-acting beta2-agonist for immediate relief. The maximum benefit may not be achieved for 1 week or longer after beginning treatment. Individual patients may experience a variable time to onset and degree of symptom relief.

Adult and Adolescent Patients Aged 12 Years and Older

For patients 12 years of age and older, the dosage is either 2 inhalations twice daily of ASMANEX HFA 100 mcg or 200 mcg. The starting dosage is based on previous asthma therapy and disease severity, including considerations of the patients' current control of asthma symptoms and risk of future exacerbations. The recommended starting dosage for patients 12 years of age and older who are not on an inhaled corticosteroid is ASMANEX HFA 100 mcg, 2 inhalations twice daily. It is recommended that patients currently receiving chronic oral corticosteroid therapy (e.g., prednisone) begin with ASMANEX HFA 200 mcg (2 inhalations twice daily). For patients who do not respond adequately to the initial dosage after 2 weeks of therapy, increasing the dosage may provide additional asthma control. The maximum daily recommended dose is two inhalations of ASMANEX HFA 200 mcg twice daily (maximum of 800 mcg a day).

After asthma stability has been achieved, it may be desirable to titrate to the lowest effective dosage to reduce the possibility of side effects.

If a dosage regimen of ASMANEX HFA fails to provide adequate control of asthma, re-evaluate the therapeutic regimen and consider additional therapeutic options, e.g., replacing the current strength of ASMANEX HFA with a higher strength, initiating an inhaled corticosteroid and long-acting beta2-agonist combination product, or initiating oral corticosteroids.

Pediatric Patients Aged 5 to Less Than 12 Years

For patients aged 5 to less than 12 years, the dosage is 2 inhalations of ASMANEX HFA 50 mcg twice daily. The maximum daily dosage is 200 mcg.

3 DOSAGE FORMS AND STRENGTHS

ASMANEX HFA is a pressurized metered dose inhaler (MDI) that is available in 2 strengths (100 mcg and 200 mcg) for adult and adolescent patients aged 12 years and older; and 1 strength (50 mcg) for pediatric patients aged 5 to less than 12 years.

ASMANEX HFA 50 mcg delivers 50 mcg of mometasone furoate per actuation.

ASMANEX HFA 100 mcg delivers 100 mcg of mometasone furoate per actuation.

ASMANEX HFA 200 mcg delivers 200 mcg of mometasone furoate per actuation.

Each strength of ASMANEX HFA is supplied with a blue colored actuator and pink dust cap [see How Supplied/Storage and Handling (16.1)].

4 CONTRAINDICATIONS

4.1 Status Asthmaticus

ASMANEX HFA is contraindicated in the primary treatment of status asthmaticus or other acute episodes of asthma where intensive measures are required.

4.2 Hypersensitivity

ASMANEX HFA is contraindicated in patients with known hypersensitivity to mometasone furoate or any of the ingredients in ASMANEX HFA [see Warnings and Precautions (5.8)].

5 WARNINGS AND PRECAUTIONS

5.1 Deterioration of Asthma and Acute Episodes

ASMANEX HFA is not indicated for the relief of acute symptoms, i.e., as rescue therapy for the treatment of acute episodes of bronchospasm. An inhaled, short-acting beta2-agonist, not ASMANEX HFA, should be used to relieve acute symptoms such as shortness of breath. When prescribing ASMANEX HFA, the physician must also provide the patient with an inhaled, short-acting beta2-agonist (e.g., albuterol) for treatment of acute symptoms, despite regular twice-daily (morning and evening) use of ASMANEX HFA. Instruct patients to contact their physician immediately if episodes of asthma that are not responsive to bronchodilators occur during the course of treatment with ASMANEX HFA. During such episodes, patients may require therapy with oral corticosteroids.

5.2 Local Effects

In clinical trials, the development of localized infections of the mouth and pharynx with Candida albicans have occurred in patients treated with ASMANEX HFA. If oropharyngeal candidiasis develops, treat with appropriate local or systemic (i.e., oral) antifungal therapy while remaining on treatment with ASMANEX HFA therapy, but at times therapy with ASMANEX HFA may need to be interrupted. To reduce the risk of oropharyngeal candidiasis, after dosing with ASMANEX HFA, advise patients to rinse their mouth with water and spit out the contents without swallowing.

5.3 Immunosuppression

Persons who are using drugs that suppress the immune system are more susceptible to infections than healthy individuals.

Chickenpox and measles, for example, can have a more serious or even fatal course in susceptible children or adults using corticosteroids. In such children or adults who have not had these diseases or who are not properly immunized, particular care should be taken to avoid exposure. How the dose, route, and duration of corticosteroid administration affect the risk of developing a disseminated infection is not known. The contribution of the underlying disease and/or prior corticosteroid treatment to the risk is also not known. If exposed to chickenpox, prophylaxis with varicella zoster immune globulin (VZIG) or pooled intravenous immunoglobulin (IVIG) may be indicated. If exposed to measles, prophylaxis with pooled intramuscular immunoglobulin (IG) may be indicated. (See the respective package inserts for complete VZIG and IG prescribing information.) If chickenpox develops, treatment with antiviral agents may be considered.

Inhaled corticosteroids should be used with caution, if at all, in patients with active or quiescent tuberculosis infection of the respiratory tract, untreated systemic fungal, bacterial, viral, or parasitic infections; or ocular herpes simplex.

5.4 Transferring Patients from Systemic Corticosteroid Therapy

Particular care is needed for patients who are transferred from systemically active corticosteroids to ASMANEX HFA because deaths due to adrenal insufficiency have occurred in asthmatic patients during and after transfer from systemic corticosteroids to less systemically available inhaled corticosteroids. After withdrawal from systemic corticosteroids, a number of months are required for recovery of hypothalamic-pituitary-adrenal (HPA) function.

Patients who have been previously maintained on 20 mg or more per day of prednisone (or its equivalent) may be most susceptible, particularly when their systemic corticosteroids have been almost completely withdrawn. During this period of HPA suppression, patients may exhibit signs and symptoms of adrenal insufficiency when exposed to trauma, surgery, or infection (particularly gastroenteritis) or other conditions associated with severe electrolyte loss. Although ASMANEX HFA may improve control of asthma symptoms during these episodes, in recommended doses it supplies less than normal physiological amounts of corticosteroid systemically and does NOT provide the mineralocorticoid activity necessary for coping with these emergencies.

During periods of stress or severe asthma attack, patients who have been withdrawn from systemic corticosteroids should be instructed to resume oral corticosteroids (in large doses) immediately and to contact their physicians for further instruction. These patients should also be instructed to carry a medical identification card indicating that they may need supplementary systemic corticosteroids during periods of stress or severe asthma attack.

Patients requiring oral or other systemic corticosteroids should be weaned slowly from oral or other systemic corticosteroid use after transferring to ASMANEX HFA. Lung function (FEV1 or PEF), beta-agonist use, and asthma symptoms should be carefully monitored during withdrawal of oral or other systemic corticosteroids. In addition to monitoring asthma signs and symptoms, patients should be observed for signs and symptoms of adrenal insufficiency such as fatigue, lassitude, weakness, nausea and vomiting, and hypotension.

Transfer of patients from systemic corticosteroid therapy to ASMANEX HFA may unmask allergic conditions previously suppressed by the systemic corticosteroid therapy, e.g., rhinitis, conjunctivitis, eczema, arthritis, and eosinophilic conditions.

During withdrawal from oral corticosteroids, some patients may experience symptoms of systemically active corticosteroid withdrawal, e.g., joint and/or muscular pain, lassitude, and depression, despite maintenance or even improvement of respiratory function.

5.5 Hypercorticism and Adrenal Suppression

ASMANEX HFA will often help control asthma symptoms with less suppression of HPA function than therapeutically equivalent oral doses of prednisone. Since mometasone furoate is absorbed into the circulation and can be systemically active at higher doses, the beneficial effects of ASMANEX HFA in minimizing HPA dysfunction may be expected only when recommended dosages are not exceeded and individual patients are titrated to the lowest effective dose.

Because of the possibility of systemic absorption of inhaled corticosteroids, patients treated with ASMANEX HFA should be observed carefully for any evidence of systemic corticosteroid effects. Particular care should be taken in observing patients postoperatively or during periods of stress for evidence of inadequate adrenal response.

It is possible that systemic corticosteroid effects such as hypercorticism and adrenal suppression (including adrenal crisis) may appear in a small number of patients, particularly when mometasone furoate is administered at higher than recommended doses over prolonged periods of time. If such effects occur, the dosage of ASMANEX HFA should be reduced slowly, consistent with accepted procedures for reducing systemic corticosteroids and for management of asthma symptoms.

5.6 Drug Interactions with Strong Cytochrome P450 3A4 Inhibitors

Caution should be exercised when considering the coadministration of ASMANEX HFA with ketoconazole, and other known strong cytochrome P450 (CYP) isoenzyme 3A4 (CYP3A4) inhibitors (e.g., ritonavir, cobicistat-containing products, atazanavir, clarithromycin, indinavir, itraconazole, nefazodone, nelfinavir, saquinavir, telithromycin) because adverse effects related to increased systemic exposure to mometasone furoate may occur [see Drug Interactions (7.1) and Clinical Pharmacology (12.3)].

5.7 Paradoxical Bronchospasm and Upper Airway Symptoms

ASMANEX HFA may produce inhalation induced bronchospasm with an immediate increase in wheezing after dosing that may be life-threatening. If inhalation induced bronchospasm occurs, it should be treated immediately with an inhaled, short-acting bronchodilator. ASMANEX HFA should be discontinued immediately and alternative therapy instituted.

5.8 Hypersensitivity Reactions Including Anaphylaxis

Hypersensitivity reactions such as urticaria, flushing, allergic dermatitis, and bronchospasm, may occur after administration of ASMANEX HFA. Discontinue ASMANEX HFA if such reactions occur [see Contraindications (4.2)].

The following additional hypersensitivity reactions, such as rash, pruritus, angioedema, and anaphylactic reaction, have been reported after administration of mometasone furoate dry powder inhaler (DPI) [see Adverse Reactions (6.2)].

5.9 Reduction in Bone Mineral Density

Decreases in bone mineral density (BMD) have been observed with long-term administration of products containing inhaled corticosteroids, including mometasone furoate. The clinical significance of small changes in BMD with regard to long-term outcomes, such as fracture, is unknown. Patients with major risk factors for decreased bone mineral content, such as prolonged immobilization, family history of osteoporosis, or chronic use of drugs that can reduce bone mass (e.g., anticonvulsants and corticosteroids) should be monitored and treated with established standards of care.

In a 2-year double-blind study in 103 male and female asthma patients 18 to 50 years of age previously maintained on bronchodilator therapy (Baseline FEV1 85%-88% predicted), treatment with mometasone furoate dry powder inhaler 200 mcg twice daily resulted in significant reductions in lumbar spine (LS) BMD at the end of the treatment period compared to placebo. The mean change from Baseline to Endpoint in the lumbar spine BMD was -0.015 (-1.43%) for the mometasone furoate dry powder inhaler group compared to 0.002 (0.25%) for the placebo group. In another 2-year double-blind study in 87 male and female asthma patients 18 to 50 years of age previously maintained on bronchodilator therapy (Baseline FEV1 82%-83% predicted), treatment with mometasone furoate dry powder inhaler 400 mcg twice daily demonstrated no statistically significant changes in lumbar spine BMD at the end of the treatment period compared to placebo. The mean change from Baseline to Endpoint in the lumbar spine BMD was -0.018 (-1.57%) for the mometasone furoate group compared to -0.006 (-0.43%) for the placebo group.

5.10 Effect on Growth

Orally inhaled corticosteroids, including ASMANEX HFA, may cause a reduction in growth velocity when administered to pediatric patients. Monitor the growth of pediatric patients receiving ASMANEX HFA routinely (e.g., via stadiometry). To minimize the systemic effects of orally inhaled corticosteroids, including ASMANEX HFA, titrate each patient's dose to the lowest dosage that effectively controls his/her symptoms [see Use in Specific Populations (8.4)].

5.11 Glaucoma and Cataracts

Glaucoma, increased intraocular pressure, and cataracts have been reported following the use of long-term administration of inhaled corticosteroids, including mometasone furoate. Consider referral to an ophthalmologist in patients who develop ocular symptoms or use ASMANEX HFA long term [see Adverse Reactions (6)].

6 ADVERSE REACTIONS

Systemic and local corticosteroid use may result in the following:

- Candida albicans infection [see Warnings and Precautions (5.2)]
- Immunosuppression [see Warnings and Precautions (5.3)]
- Hypercorticism and adrenal suppression [see Warnings and Precautions (5.5)]
- Growth effects in pediatrics [see Warnings and Precautions (5.10)]
- Glaucoma and cataracts [see Warnings and Precautions (5.11)]

Because clinical trials are conducted under widely varying conditions, adverse reaction rates observed in the clinical trials of a drug cannot be directly compared to rates in the clinical trials of another drug and may not reflect the rates observed in practice.

6.1 Clinical Trials Experience

Adult and Adolescent Patients Aged 12 Years and Older

The safety of ASMANEX HFA was evaluated in 2 randomized placebo and active-controlled trials of 12 and 26 weeks' duration, conducted as part of a mometasone furoate/formoterol fumarate combination product asthma program, which enrolled 1509 patients with persistent asthma. Patient ages ranged from 12 to 84 years of age, 41% were male and 59% female, 73% were Caucasian and 27% non-Caucasian. Of the total population enrolled in the 2 trials, 432 patients received two inhalations twice daily of either ASMANEX HFA, 100 mcg or 200 mcg/actuation. In the 26-week trial (Trial 1) 192 patients received two inhalations twice daily of ASMANEX HFA 100 mcg/actuation and 196 patients received placebo. In the 12 week trial (Trial 2) 240 patients received two inhalations twice daily of ASMANEX HFA 200 mcg/actuation and 233 and 255 patients received mometasone furoate and formoterol fumarate 100 mcg/5 mcg and 200 mcg/5 mcg/actuation combination products, respectively, as comparators.

In these trials, the proportion of patients who discontinued study treatment early due to adverse reactions was 3% and 2% for ASMANEX HFA 100 and 200 mcg treated patients, respectively, and 4% for placebo-treated patients. Serious adverse reactions, whether considered drug-related or not by the investigators, which occurred more frequently in ASMANEX HFA-treated patients included colitis ulcerative, colonic polyp, chest pain, gastroenteritis, endometriosis, asthma, and hemoptysis; all events occurred at rates less than 1%.

The incidence of treatment emergent adverse events associated with ASMANEX HFA are shown in Tables 1 and 2. These are based upon data from each of the 2 clinical trials of 12 or 26 weeks in duration in patients 12 years and older treated with two inhalations twice daily of ASMANEX HFA (100 mcg or 200 mcg), mometasone furoate/formoterol fumarate (100 mcg/5 mcg or 200 mcg/5 mcg), or placebo.

TABLE 1: Trial 1: Treatment-Emergent Adverse Events Occurring at an Incidence of ≥3% and More Commonly than Placebo Over 26 Weeks
 | ASMANEX HFA 100 mcg N=192 n (%) | Placebo N=196 n (%)
Nasopharyngitis | 15 (8) | 7 (4)
Headache | 10 (5) | 7 (4)
Influenza | 7 (4) | 5 (3)
Sinusitis | 6 (3) | 2 (1)

TABLE 2: Trial 2: Treatment-Emergent Adverse Events Occurring at an Incidence of ≥3% Over 12 Weeks
 | ASMANEX HFA 200 mcg N=240 n (%) | MF/F [MF/F = mometasone furoate/formoterol fumarate.] 100/5 mcg N=233 n (%) | MF/F 200/5 mcg N=255 n (%)
Nasopharyngitis | 13 (5) | 8 (3) | 12 (5)
Headache | 8 (3) | 10 (4) | 5 (2)
Bronchitis | 6 (3) | 2 (1) | 7 (3)

Oral candidiasis has been reported in clinical trials at an incidence of 0.5% in patients using ASMANEX HFA 100 mcg, 0.8% in patients using ASMANEX HFA 200 mcg and 0.5% in the placebo group.

Pediatric Patients Aged 5 to Less Than 12 Years

The safety profile for ASMANEX HFA 50 mcg, 2 inhalations twice daily, is based on two clinical trials consisting of a total of 759 patients aged 5 to less than 12 years with persistent asthma. The first trial was a placebo-controlled trial comparing ASMANEX HFA 50 mcg (administered as 2 inhalations, twice daily) to 2 other dosage strengths of mometasone furoate MDI (25 mcg or 100 mcg, each administered as two inhalations, twice daily) as well as mometasone furoate DPI 100 mcg, administered as one evening inhalation. The second trial compared ASMANEX HFA 50 mcg to the combination of mometasone furoate and formoterol fumarate 50 mcg/5 mcg, each administered by MDI as two inhalations, twice daily.

Overall, the safety profile for pediatric patients is similar to that observed in patients aged 12 years and older.

6.2 Postmarketing Experience

There are no postmarketing adverse experiences reported to date with ASMANEX HFA. However, the postmarketing safety experience with mometasone furoate dry powder inhaler is relevant to ASMANEX HFA since they contain the same active ingredient. The following adverse reactions have been reported during post-approval use of mometasone furoate dry powder inhaler. Because these reactions are reported voluntarily from a population of uncertain size, it is not always possible to reliably estimate their frequency or establish a causal relationship to drug exposure.

Eye Disorders: Vision blurred [see Warnings and Precautions (5.11)].

Immune System Disorders: Immediate and delayed hypersensitivity reactions including rash, pruritus, angioedema and anaphylactic reaction [see Contraindications (4.2) and Warnings and Precautions (5.8)].

Respiratory, Thoracic and Mediastinal Disorders: Asthma aggravation, which may include cough, dyspnea, wheezing and bronchospasm.

7 DRUG INTERACTIONS

In clinical trials, concurrent administration of ASMANEX HFA and other drugs, such as short-acting beta2-agonist and intranasal corticosteroids have not resulted in an increased frequency of adverse drug reactions. No formal drug interaction studies have been performed with ASMANEX HFA.

7.1 Inhibitors of Cytochrome P450 3A4

The main route of metabolism of corticosteroids, including mometasone furoate, is via CYP3A4. After oral administration of ketoconazole, a strong inhibitor of CYP3A4, the mean plasma concentration of orally inhaled mometasone furoate increased. Concomitant administration of CYP3A4 inhibitors may inhibit the metabolism of, and increase the systemic exposure to, mometasone furoate and potentially increase the risk for systemic corticosteroid side effects. Caution should be exercised when considering the coadministration of ASMANEX HFA with long-term ketoconazole and other known strong CYP3A4 inhibitors (e.g., ritonavir, cobicistat-containing products, atazanavir, clarithromycin, indinavir, itraconazole, nefazodone, nelfinavir, saquinavir, telithromycin) [see Warnings and Precautions (5.6) and Clinical Pharmacology (12.3)]. Consider the benefit of coadministration versus the potential risk of systemic corticosteroid effects, in which case patients should be monitored for systemic corticosteroid side effects.

8 USE IN SPECIFIC POPULATIONS

8.1 Pregnancy

Risk Summary

There are no randomized clinical studies of ASMANEX HFA in pregnant women. There are clinical considerations with the use of ASMANEX HFA in pregnant women [see Clinical Considerations]. In animal reproduction studies with pregnant mice, rats, or rabbits, mometasone furoate caused increased fetal malformations and decreased fetal survival and growth following administration of doses that produced exposures approximately 1/3 to 8 times the maximum recommended human dose (MRHD) on a mcg/m^2 or AUC basis [see Data]. However, experience with oral corticosteroids suggests that rodents are more prone to teratogenic effects from corticosteroid exposure than humans.

The estimated background risk of major birth defects and miscarriage for the indicated population is unknown. In the U.S. general population, the estimated risk of major birth defects and miscarriage in clinically recognized pregnancies is 2 to 4% and 15 to 20%, respectively.

Clinical Considerations

Disease-associated maternal and/or embryo/fetal risk

In women with poorly or moderately controlled asthma, there is an increased risk of several perinatal adverse outcomes such as preeclampsia in the mother and prematurity, low birth weight, and small for gestational age in the neonate. Pregnant women with asthma should be closely monitored and medication adjusted as necessary to maintain optimal asthma control.

Data

Animal Data

In an embryofetal development study with pregnant mice dosed throughout the period of organogenesis, mometasone furoate produced cleft palate at an exposure approximately one-third of the MRHD (on a mcg/m^2 basis with maternal subcutaneous doses of 60 mcg/kg and above) and decreased fetal survival at an exposure approximately equivalent to the MRHD (on a mcg/m^2 basis with a maternal subcutaneous dose of 180 mcg/kg). No toxicity was observed with a dose that produced an exposure approximately one-tenth of the MRHD (on a mcg/m^2 basis with maternal topical dermal doses of 20 mcg/kg and above).

In an embryofetal development study with pregnant rats dosed throughout the period of organogenesis, mometasone furoate produced fetal umbilical hernia at exposures approximately 6 times the MRHD (on a mcg/m^2 basis with maternal topical dermal doses of 600 mcg/kg and above) and delays in fetal ossification at exposures approximately 3 times the MRHD (on a mcg/m^2 basis with maternal topical dermal doses of 300 mcg/kg and above).

In another reproductive toxicity study, pregnant rats were dosed with mometasone furoate throughout pregnancy or late in gestation. Treated animals had prolonged and difficult labor, fewer live births, lower birth weight, and reduced early pup survival at an exposure that was approximately 8 times the MRHD (on an area under the curve (AUC) basis with a maternal subcutaneous dose of 15 mcg/kg). There were no findings with an exposure approximately 4 times the MRHD (on an AUC basis with a maternal subcutaneous dose of 7.5 mcg/kg).

Embryofetal development studies were conducted with pregnant rabbits dosed with mometasone furoate by either the topical dermal route or oral route throughout the period of organogenesis. In the study using the topical dermal route, mometasone furoate caused multiple malformations in fetuses (e.g., flexed front paws, gallbladder agenesis, umbilical hernia, hydrocephaly) at an exposure approximately 3 times the MRHD (on a mcg/m^2 basis with maternal topical dermal doses of 150 mcg/kg and above). In the study using the oral route, mometasone furoate caused increased fetal resorptions and cleft palate and/or head malformations (hydrocephaly and domed head) at an exposure approximately 1/2 of the MRHD (on AUC basis with a maternal oral dose of 700 mcg/kg). At an exposure approximately 2 times the MRHD (on an AUC basis with a maternal oral dose of 2800 mcg/kg), most litters were aborted or resorbed. No effects were observed at an exposure approximately 1/10 of the MRHD (on an AUC basis with a maternal oral dose of 140 mcg/kg).

8.2 Lactation

Risk Summary

There are no available data on the presence of ASMANEX HFA in human milk, the effects on the breastfed child, or the effects on milk production. Other inhaled corticosteroids, similar to mometasone furoate, are present in human milk. The developmental and health benefits of breastfeeding should be considered along with the mother's clinical need for ASMANEX HFA and any potential adverse effects on the breastfed infant from ASMANEX HFA or from the underlying maternal condition.

8.4 Pediatric Use

The safety and effectiveness of ASMANEX HFA have been established in patients 12 years of age and older in 2 clinical trials of 12 and 26 weeks in duration. In the 2 clinical trials, 32 patients 12 to 17 years of age were treated with ASMANEX HFA. No overall differences in effectiveness were observed between patients in this age group compared to those observed in patients 18 years of age and older. There were no obvious differences in the type or frequency of adverse reactions reported in this age group compared to patients 18 years of age and older.

The safety and effectiveness of ASMANEX HFA 50 mcg, two inhalations twice daily, have been established in patients with asthma aged 5 to less than 12 years in clinical trials up to 24 weeks of treatment duration. The safety profile and overall effectiveness in this age group were consistent with that observed in patients aged 12 years and older who also received ASMANEX HFA [see Adverse Reactions (6.1) and Clinical Studies (14.1)].

The safety and effectiveness of ASMANEX HFA have not been established in children younger than 5 years of age.

Controlled clinical studies have shown that inhaled corticosteroids may cause a reduction in growth velocity in pediatric patients. In these studies, the mean reduction in growth velocity was approximately 1 cm per year (range 0.3 to 1.8 per year) and appears to depend upon dose and duration of exposure. This effect was observed in the absence of laboratory evidence of HPA axis suppression, suggesting that growth velocity is a more sensitive indicator of systemic corticosteroid exposure in pediatric patients than some commonly used tests of HPA axis function. The long-term effects of this reduction in growth velocity associated with orally inhaled corticosteroids, including the impact on final adult height, are unknown. The potential for "catch-up" growth following discontinuation of treatment with orally inhaled corticosteroids has not been adequately studied.

The growth of children and adolescents receiving orally inhaled corticosteroids, including ASMANEX HFA, should be monitored routinely (e.g., via stadiometry). If a child or adolescent on any corticosteroid appears to have growth suppression, the possibility that he/she is particularly sensitive to this effect should be considered. The potential growth effects of prolonged treatment should be weighed against clinical benefits obtained and the risks associated with alternative therapies. To minimize the systemic effects of orally inhaled corticosteroids, including ASMANEX HFA, each patient should be titrated to his/her lowest effective dose [see Dosage and Administration (2.2)].

8.5 Geriatric Use

A total of 38 patients 65 years of age and older (3 of whom were 75 years and older) have been treated with ASMANEX HFA in 2 clinical trials of 12 and 26 weeks in duration. No overall differences in safety or effectiveness were observed between these patients and younger patients, but greater sensitivity of some older individuals cannot be ruled out. Based on available data for ASMANEX HFA, no adjustment of dosage in geriatric patients is warranted.

8.6 Hepatic Impairment

Concentrations of mometasone furoate appear to increase with severity of hepatic impairment [see Clinical Pharmacology (12.3)].

10 OVERDOSAGE

Chronic overdosage may result in signs/symptoms of hypercorticism [see Warnings and Precautions (5.5)]. Single oral doses up to 8000 mcg of mometasone furoate have been studied on adult subjects with no adverse reactions reported.

11 DESCRIPTION

ASMANEX HFA is a metered dose inhaler for oral inhalation only, consisting of 50 mcg, 100 mcg, or 200 mcg of mometasone furoate per actuation.

Mometasone furoate, the active component of ASMANEX HFA, is a corticosteroid having the chemical name 9,21-dichloro-11(Beta),17-dihydroxy-16 (alpha)-methylpregna-1,4-diene-3,20-dione 17-(2-furoate) with the following chemical structure:

Mometasone furoate is a white powder with an empirical formula of C27H30Cl2O6, and molecular weight 521.44. It is practically insoluble in water; slightly soluble in methanol, ethanol, and isopropanol; soluble in acetone.

ASMANEX HFA 50 mcg, 100 mcg, and 200 mcg are each formulated as a hydrofluoroalkane (HFA-227: 1,1,1,2,3,3,3-heptafluoropropane) propelled pressurized metered dose inhaler containing sufficient amount of drug for 120 actuations [see How Supplied/Storage and Handling (16)]. After priming, each actuation of the inhaler delivers 60, 115, or 225 mcg of mometasone furoate in 69.6 mg of suspension from the valve and delivers 50, 100, or 200 mcg of mometasone furoate from the actuator. The actual amount of drug delivered to the lung may depend on patient factors, such as the coordination between actuation of the device and inspiration through the delivery system. ASMANEX HFA also contains ethanol as a cosolvent and oleic acid as a surfactant.

ASMANEX HFA should be primed before using for the first time by releasing 4 test sprays into the air, away from the face, shaking well before each spray. In cases where the inhaler has not been used for more than 5 days, prime the inhaler again by releasing 4 test sprays into the air, away from the face, shaking well before each spray.

12 CLINICAL PHARMACOLOGY

12.1 Mechanism of Action

Mometasone furoate is a corticosteroid demonstrating potent anti-inflammatory activity. The precise mechanism of corticosteroid action on asthma is not known. Inflammation is an important component in the pathogenesis of asthma. Corticosteroids have been shown to have a wide range of inhibitory effects on multiple cell types (e.g., mast cells, eosinophils, neutrophils, macrophages, and lymphocytes) and mediators (e.g., histamine, eicosanoids, leukotrienes, and cytokines) involved in inflammation and in the asthmatic response. These anti-inflammatory actions of corticosteroids may contribute to their efficacy in asthma.

Mometasone furoate has been shown in vitro to exhibit a binding affinity for the human glucocorticoid receptor, which is approximately 12 times that of dexamethasone, 7 times that of triamcinolone acetonide, 5 times that of budesonide, and 1.5 times that of fluticasone. The clinical significance of these findings is unknown.

12.2 Pharmacodynamics

Systemic effects of inhaled corticosteroids are related to systemic exposure. Pharmacokinetic data have demonstrated that, in adults, systemic exposure to mometasone furoate administered by MDI is the same or lower than that of equivalent doses of inhaled mometasone furoate administered via DPI [see Clinical Pharmacology (12.3)]. Based upon the pharmacokinetic data, the systemic effects (e.g., HPA-axis suppression and growth retardation) of mometasone furoate delivered by MDI in adult and pediatric patients would be expected to be no greater than what is reported for inhaled mometasone furoate when administered at comparable doses via DPI [see Use in Specific Populations (8.4)].

HPA Axis Effects (Adults)

The effects of inhaled mometasone furoate administered via ASMANEX HFA on adrenal function have not been directly evaluated. However, the effects of inhaled mometasone furoate, administered as part of a mometasone furoate/formoterol fumarate inhalation aerosol combination product, on adrenal function were evaluated in two clinical trials in patients with asthma. As no evidence of a pharmacokinetic drug interaction between mometasone furoate and formoterol was observed when the two drugs were administered in combination, the HPA axis effects from the combination product are applicable to ASMANEX HFA. For the mometasone furoate/formoterol fumarate combination product clinical program, HPA-axis function was assessed by 24-hour plasma cortisol AUC. Although both these trials have open-label design and contain a small number of subjects per treatment arm, results from these trials taken together demonstrated suppression of 24-hour plasma cortisol AUC for the combination mometasone furoate/formoterol fumarate 200 mcg/5 mcg compared to placebo consistent with the known systemic effects of inhaled corticosteroid.

In a 42-day, open-label, placebo- and active-controlled study, the mean change from baseline plasma cortisol AUC(0-24 hr) was 8%, 22% and 34% lower compared to placebo for the mometasone furoate/formoterol fumarate 100 mcg/5 mcg (n=13), mometasone furoate/formoterol fumarate 200 mcg/5 mcg (n=15) and fluticasone propionate/salmeterol xinafoate 230 mcg/21 mcg (n=16) treatment groups, respectively.

In a 52-week, open-label safety study, the mean plasma cortisol AUC(0-24 hr) was 2.2%, 29.6%, 16.7%, and 32.2% lower from baseline for the mometasone furoate/formoterol fumarate 100 mcg/5 mcg (n=18), mometasone furoate/formoterol fumarate 200 mcg/5 mcg (n=20), fluticasone propionate/salmeterol xinafoate 125/25 mcg (n=8), and fluticasone propionate/salmeterol xinafoate 250/25 mcg (n=11) treatment groups, respectively.

The potential effect of mometasone furoate via a dry powder inhaler (DPI) on the HPA axis was also assessed in a 29-day study. A total of 64 adult patients with mild to moderate asthma were randomized to one of 4 treatment groups: mometasone furoate DPI 440 mcg twice daily, mometasone furoate DPI 880 mcg twice daily, oral prednisone 10 mg once daily, or placebo. The 30-minute post-Cosyntropin stimulation serum cortisol concentration on Day 29 was 23.2 mcg/dL for the mometasone furoate DPI 440 mcg twice daily group and 20.8 mcg/dL for the mometasone furoate DPI 880 mcg twice daily group, compared to 14.5 mcg/dL for the oral prednisone 10 mg group and 25 mcg/dL for the placebo group. The difference between mometasone furoate DPI 880 mcg twice daily (twice the maximum recommended dose) and placebo was statistically significant.

HPA Axis Effects (Pediatrics)

The potential effect of mometasone furoate via a DPI on the HPA axis was assessed in 50 children aged 6 to 11 years in a 29-day, randomized, double-blind, placebo-controlled, parallel-group clinical trial. In this study, the mean difference from placebo in plasma cortisol AUC(0-12hr) for DPI 110 mcg twice daily was 3.4 mcg∙hr/dL (95% CI: -14.0, 20.7) and for 220 mcg twice daily was -16.0 mcg∙hr/dL (95% CI: -33.9, 1.9). The mean difference from placebo in plasma cortisol AUC(0-12hr) for the 440 mcg twice daily group (eight times the currently recommended mometasone furoate dose via a DPI in children ages 4-11) was -17.9 mcg∙hr/dL (95% CI: -35.8, 0.0). The mean differences in urinary-free cortisol changes from baseline compared to placebo were 3.1 mcg/day (95% CI: -3.3, 9.6), 3.3 mcg/day (95% CI: -3.0, 9.7), and -2.0 mcg/day (95% CI: -8.6, 4.6) for the groups treated with 110 mcg twice daily, 220 mcg twice daily, and 440 mcg twice daily, respectively.

12.3 Pharmacokinetics

As no evidence of a pharmacokinetic drug interaction between mometasone furoate and formoterol was observed when the two drugs were administered from a mometasone furoate/formoterol fumarate combination product, the pharmacokinetics information from the combination product is applicable to ASMANEX HFA.

Absorption

Adult Healthy Subjects: Following oral inhalation of single doses of ASMANEX HFA, mometasone furoate was absorbed in healthy subjects with median Tmax values ranging from 0.50 to 2 hours. Following single-dose administration of higher than recommended dose of ASMANEX HFA (4 inhalations of ASMANEX HFA 200 mcg) in healthy subjects, the arithmetic mean (CV%) Cmax and AUC(0-tf) values for mometasone furoate were 53 (102) pg/mL and 992 (80) pg∙hr/mL, respectively. Studies using oral dosing of labeled and unlabeled drug have demonstrated that the oral systemic bioavailability of mometasone furoate is negligible (<1%).

Following single-dose administration of a higher than recommended dose of mometasone furoate (4 inhalations of mometasone furoate/formoterol fumarate 200 mcg/5 mcg) in healthy subjects, the arithmetic mean (CV%) Cmax and AUC(0-12 hr) values for mometasone furoate were 67.8 (49) pg/mL and 650 (51) pg∙hr/mL, respectively, while the corresponding estimates following 5 days of BID dosing with mometasone furoate 800 mcg/20 mcg were 241 (36) pg/mL and 2200 (35) pg∙hr/mL. The systemic exposure to mometasone furoate (based on AUC) was approximately 52% and 25% lower on Day 1 and Day 5, respectively, following mometasone furoate administration compared to mometasone furoate via a DPI.

Adult Asthma Patients: Following oral inhalation of single and multiple doses of the mometasone furoate/formoterol fumarate combination product, mometasone furoate was absorbed in asthma patients with median Tmax values ranging from 1 to 2 hours. Following single-dose administration of mometasone furoate/formoterol fumarate 400 mcg/10 mcg, the arithmetic mean (CV%) Cmax and AUC(0-12 hr) values for mometasone furoate were 20 (88) pg/mL and 170 (94) pg∙hr/mL, respectively, while the corresponding estimates following twice daily dosing of mometasone furoate/formoterol fumarate 400 mcg/10 mcg at steady-state were 60 (36) pg/mL and 577 (40) pg∙hr/mL.

Distribution

Based on the study employing a 1000 mcg inhaled dose of tritiated mometasone furoate inhalation powder in humans, no appreciable accumulation of mometasone furoate in the red blood cells was found. Following an intravenous 400 mcg dose of mometasone furoate, the plasma concentrations showed a biphasic decline, with a mean steady-state volume of distribution of 152 liters. The in vitro protein binding for mometasone furoate was reported to be 98% to 99% (in a concentration range of 5 to 500 ng/mL).

Metabolism

Studies have shown that mometasone furoate is primarily and extensively metabolized in the liver of all species investigated and undergoes extensive metabolism to multiple metabolites. In vitro studies have confirmed the primary role of human liver CYP3A4 in the metabolism of this compound; however, no major metabolites were identified. Human liver CYP3A4 metabolizes mometasone furoate to 6-beta hydroxy mometasone furoate.

Excretion

Following an intravenous dosing, the terminal half-life was reported to be about 5 hours. Following the inhaled dose of tritiated 1000 mcg mometasone furoate, the radioactivity is excreted mainly in the feces (a mean of 74%), and to a small extent in the urine (a mean of 8%) up to 7 days. No radioactivity was associated with unchanged mometasone furoate in the urine. Absorbed mometasone furoate is cleared from plasma at a rate of approximately 12.5 mL/min/kg, independent of dose. The effective t½ for mometasone furoate following inhalation was 25 hours in adult healthy subjects and in adult patients with asthma.

Special Populations

Hepatic/Renal Impairment: There are no data regarding the specific use of ASMANEX HFA in patients with hepatic or renal impairment.

A study evaluating the administration of a single inhaled dose of 400 mcg mometasone furoate by a dry powder inhaler to adult subjects with mild (n=4), moderate (n=4), and severe (n=4) hepatic impairment resulted in only 1 or 2 subjects in each group having detectable peak plasma concentrations of mometasone furoate (ranging from 50-105 pg/mL). The observed peak plasma concentrations appear to increase with severity of hepatic impairment; however, the numbers of detectable levels were few.

Gender and Race: Specific studies to examine the effects of gender and race on the pharmacokinetics of ASMANEX HFA have not been specifically studied.

Geriatrics: The pharmacokinetics of ASMANEX HFA have not been specifically studied in the elderly population.

Drug-Drug Interactions

A single-dose crossover study was conducted to compare the pharmacokinetics of 4 inhalations of the following: mometasone furoate MDI, formoterol MDI, mometasone furoate/formoterol fumarate MDI combination product, and mometasone furoate MDI plus formoterol fumarate MDI administered concurrently. The results of the study indicated that there was no evidence of a pharmacokinetic interaction between mometasone furoate and formoterol.

Inhibitors of Cytochrome P450 Enzymes: Ketoconazole: In a drug interaction study, an inhaled dose of mometasone furoate 400 mcg delivered by a dry powder inhaler was given to 24 adult healthy subjects twice daily for 9 days and ketoconazole 200 mg (as well as placebo) were given twice daily concomitantly on Days 4 to 9. Mometasone furoate plasma concentrations were <150 pg/mL on Day 3 prior to coadministration of ketoconazole or placebo. Following concomitant administration of ketoconazole, 4 out of 12 subjects in the ketoconazole treatment group (n=12) had peak plasma concentrations of mometasone furoate >200 pg/mL on Day 9 (211-324 pg/mL). Mometasone furoate plasma levels appeared to increase and plasma cortisol levels appeared to decrease upon concomitant administration of ketoconazole.

13 NONCLINICAL TOXICOLOGY

13.1 Carcinogenesis, Mutagenesis, Impairment of Fertility

In a 2-year carcinogenicity study in Sprague Dawley rats, mometasone furoate demonstrated no statistically significant increase in the incidence of tumors at inhalation doses up to 67 mcg/kg (approximately 14 times the MRHD on an AUC basis). In a 19-month carcinogenicity study in Swiss CD-1 mice, mometasone furoate demonstrated no statistically significant increase in the incidence of tumors at inhalation doses up to 160 mcg/kg (approximately 9 times the MRHD on an AUC basis).

Mometasone furoate increased chromosomal aberrations in an in vitro Chinese hamster ovary cell assay, but did not have this effect in an in vitro Chinese hamster lung cell assay. Mometasone furoate was not mutagenic in the Ames test or mouse lymphoma assay, and was not clastogenic in an in vivo mouse micronucleus assay, a rat bone marrow chromosomal aberration assay, or a mouse male germ-cell chromosomal aberration assay. Mometasone furoate also did not induce unscheduled DNA synthesis in vivo in rat hepatocytes.

In reproductive studies in rats, impairment of fertility was not produced by subcutaneous doses up to 15 mcg/kg (approximately 8 times the MRHD on an AUC basis).

14 CLINICAL STUDIES

14.1 Asthma

Adult and Adolescent Patients Aged 12 Years of Age and Older

The safety and efficacy of ASMANEX HFA was demonstrated in two randomized, double-blind, placebo- or active-controlled multi-center clinical trials of 12 and 26 weeks' duration, conducted as part of a mometasone furoate/formoterol fumarate 100/5 mcg or 200/5 mcg combination product development program. A total of 1509 patients 12 years of age and older with persistent asthma (mean baseline FEV1 of 66% to 73% predicted) were evaluated.

Trial 1: Clinical Trial with ASMANEX HFA 100 mcg

This 26-week, placebo-controlled trial (NCT00383240) conducted as part of a mometasone furoate/formoterol fumarate combination product asthma program evaluated 781 patients 12 years of age and older. Of these patients, 192 patients received ASMANEX HFA 100 mcg and 196 patients received placebo, each administered as 2 inhalations twice daily by metered dose inhalation aerosols. All other maintenance therapies were discontinued. The study included a 2- to 3-week run-in period with ASMANEX HFA 100 mcg, 2 inhalations twice daily. Patients ranged from 12 to 76 years of age, 41% were male and 59% female, and 72% were Caucasian and 28% non-Caucasian. Patients had persistent asthma and were not well controlled on medium dose of inhaled corticosteroids prior to randomization. Mean FEV1 and mean percent predicted FEV1 were similar among all treatment groups (2.33 L, 73%). Thirteen (7%) patients receiving ASMANEX HFA 100 mcg and 46 (23%) patients receiving placebo discontinued the study early due to treatment failure.

The change in mean trough FEV1 from baseline to Week 12 compared to placebo was assessed to evaluate the efficacy of ASMANEX HFA 100 mcg. The change from baseline to week 12 in the mean trough FEV1 was greater among patients receiving ASMANEX HFA 100 mcg 2 inhalations twice daily than among those receiving placebo (treatment difference from placebo 0.12 L and 95% confidence interval [0.05, 0.20]).

Clinically judged deteriorations in asthma or reductions in lung function were also assessed to evaluate the efficacy of ASMANEX HFA 100 mcg. Deteriorations in asthma were defined as any of the following: a 20% decrease in FEV1; a 30% decrease in PEF on two or more consecutive days; emergency treatment, hospitalization, or treatment with systemic corticosteroids or other asthma medications not allowed per protocol. Sixty-five (34%) patients who received ASMANEX HFA 100 mcg reported an event compared to 109 (56%) patients who received placebo.

Treatment of asthma patients with ASMANEX HFA 100 mcg, two inhalations twice daily also resulted in fewer nocturnal awakenings and improved morning peak flow compared to those who received placebo.

Trial 2: Clinical Trial with ASMANEX HFA 200 mcg

This 12-week randomized, double-blind, active-controlled trial (NCT00381485) also conducted as part of a mometasone furoate/formoterol fumarate combination product asthma program evaluated a total of 728 patients 12 years of age and older comparing ASMANEX HFA 200 mcg (n=240 patients), mometasone furoate/formoterol fumarate 200 mcg/5 mcg (n=255 patients), and mometasone furoate/formoterol fumarate 100 mcg/5 mcg (n=233 patients), each administered as 2 inhalations twice daily by metered dose inhalation aerosols. All other maintenance therapies were discontinued. This trial included a 2- to 3-week run-in period with ASMANEX HFA 200 mcg, 2 inhalations twice daily. Patients had persistent asthma and were uncontrolled on high-dose inhaled corticosteroids prior to study entry. Patients ranged from 12 to 84 years of age, 44% were male and 56% female, and 89% were Caucasian and 11% non-Caucasian. Mean FEV1 and mean percent predicted FEV1 values were similar among all treatment groups (2.05 L, 66%). The number of patients who discontinued the trial early due to treatment failure were 11 (5%) in the mometasone furoate/formoterol fumarate 100 mcg/5 mcg group, 8 (3%) in the mometasone furoate/formoterol fumarate 200 mcg/5 mcg group, and 13 (5%) in the ASMANEX HFA 200 mcg group.

In order to assess the added benefit of a higher dose of mometasone in the 200 mcg/actuation mometasone furoate product compared to the lower dose 100 mcg/actuation product, trough FEV1 at 12 weeks was compared between the combination mometasone furoate/formoterol fumarate 200 mcg/5 mcg and 100 mcg/5 mcg treatment groups as a secondary endpoint. Improvement in trough FEV1 from baseline to week 12 in patients who received mometasone furoate 200 mcg in combination with formoterol fumarate 5 mcg was numerically greater than among patients who received mometasone furoate 100 mcg in combination with formoterol fumarate 5 mcg (treatment difference of 0.05 L and 95% confidence interval [-0.02, 0.10]).

Other Studies in Adult and Adolescent Patients

In addition to Trial 1 and Trial 2, the safety and efficacy of mometasone furoate MDI 100 mcg and 200 mcg (each administered as 2 inhalations, twice daily), in comparison to placebo were demonstrated in two other 12-week, placebo-controlled trials which evaluated the mean change in FEV1 from baseline as a primary endpoint. A 26-week trial (NCT00383552) also evaluated the same endpoint with a lower dose of mometasone furoate MDI.

Pediatric Patients Aged 5 to Less Than 12 Years

The safety and efficacy of ASMANEX HFA were demonstrated in a 12-week, randomized, double-blind, placebo-controlled, multicenter clinical trial in a total of 583 patients aged 5 to less than 12 years with persistent asthma (mean baseline FEV1 of 79%-predicted) who had been using a low-to-medium dose of ICS with or without LABA for at least 12 weeks prior to study entry. After an approximate 2-week run-in period, subjects were randomized to ASMANEX HFA 50 mcg dose (administered as two inhalations, twice daily), two other doses of ASMANEX HFA, ASMANEX dry-powder inhaler (DPI) or placebo. Patients were 60% male, 71% were Caucasian, and 13% were aged 5 to 6 years old. Primary endpoint results show that after 12 weeks of treatment, ASMANEX HFA 50 mcg (administered as two inhalations, twice daily) was statistically superior to placebo with respect to the improvement from baseline in AM pre-dose percent predicted FEV1 at the end of the dosing interval (6.29%, 95% CI: 3.05, 9.53).

16 HOW SUPPLIED/STORAGE AND HANDLING

16.1 How Supplied

ASMANEX HFA is available in three strengths and supplied in the following package size (TABLE 3):

TABLE 3
Package | NDC | Strength Identifier (Color Band) [Included on the outer carton, actuator, and canister labels.]
ASMANEX HFA 50 mcg 120 metered actuations | 78206-111-01 | Orange
ASMANEX HFA 100 mcg 120 metered actuations | 78206-112-01 | Green
ASMANEX HFA 200 mcg 120 metered actuations | 78206-113-01 | Blue

Each strength is supplied as a pressurized aluminum canister that has a blue plastic actuator integrated with a dose counter and a pink dust cap. Each canister has a net fill weight of 13 grams. Each inhaler is placed into a carton. Each carton contains 1 inhaler.

Initially the dose counter will display "124" actuations. After the initial priming with 4 actuations, the dose counter will read "120" and the inhaler is now ready for use.

16.2 Storage and Handling

Only use the ASMANEX HFA canister with the ASMANEX HFA actuator. Do not use the ASMANEX HFA actuator with any other inhalation drug product. Do not use actuators from other products with the ASMANEX HFA canister.

Do not remove the canister from the actuator because the correct amount of medication may not be discharged; the dose counter may not function properly; reinsertion may cause the dose counter to count down by 1 and discharge a puff.

The correct amount of medication in each inhalation cannot be ensured after the labeled number of actuations from the canister has been used, even though the inhaler may not feel completely empty and may continue to operate. Discard the inhaler when the labeled number of actuations has been used (the dose counter will read "0").

Store at controlled room temperature 20°C-25°C (68°F-77°F); excursions permitted to 15°C-30°C (59°F-86°F) [see USP Controlled Room Temperature].

After priming, store the inhaler with the mouthpiece down or in a horizontal position.

For best results, keep the canister at room temperature before use. Shake well and remove the cap from the mouthpiece of the actuator before using. Keep out of reach of children. Avoid spraying in eyes.

Contents Under Pressure: Do not puncture. Do not use or store near heat or open flame. Exposure to temperatures above 120°F may cause bursting. Never throw container into fire or incinerator.

17 PATIENT COUNSELING INFORMATION

Advise the patient to read the FDA-approved patient labeling (Patient Information and Instructions for Use).

Not for Acute Symptoms

Advise patients that ASMANEX HFA is not indicated to relieve acute asthma symptoms, and extra doses should not be used for that purpose. ASMANEX HFA is not a bronchodilator and should not be used to treat status asthmaticus or to relieve acute asthma symptoms. Treat acute asthma symptoms with an inhaled, short-acting beta2-agonist such as albuterol. Prescribe the patient with such medication and instruct the patient on how to use it [see Warnings and Precautions (5.1)].

Instruct patients to seek medical attention immediately if they experience any of the following:

- If their symptoms worsen
- Significant decrease in lung function as outlined by the physician
- If they need more inhalations of a short-acting beta2-agonist than usual

Advise patients not to increase the dose or frequency of ASMANEX HFA. Do not exceed the daily dosage of ASMANEX HFA two inhalations twice daily. If they miss a dose, instruct patients to take their next dose at the same time they normally do.

Advise patients not to stop or reduce ASMANEX HFA therapy without physician/provider guidance since symptoms may recur after discontinuation.

Local Effects

Advise patients that localized infections with Candida albicans occurred in the mouth and pharynx in some patients. If oropharyngeal candidiasis develops, treat with appropriate local or systemic (i.e., oral) antifungal therapy while still continuing with ASMANEX HFA therapy, but at times therapy with ASMANEX HFA may need to be temporarily interrupted under close medical supervision. After dosing, advise patients to rinse their mouth with water and spit out contents without swallowing [see Warnings and Precautions (5.2)].

Immunosuppression

Warn patients who are on immunosuppressant doses of corticosteroids to avoid exposure to chickenpox or measles and, if exposed, to consult their physician without delay. Inform patients of potential worsening of existing tuberculosis, fungal, bacterial, viral, or parasitic infections, or ocular herpes simplex [see Warnings and Precautions (5.3)].

Hypercorticism and Adrenal Suppression

Advise patients that ASMANEX HFA may cause systemic corticosteroid effects of hypercorticism and adrenal suppression. Additionally, instruct patients that deaths due to adrenal insufficiency have occurred during and after transfer from systemic corticosteroids. Instruct patients to slowly taper from systemic corticosteroids if transferring to ASMANEX HFA [see Warnings and Precautions (5.4 and 5.5)].

Reduction in Bone Mineral Density

Advise patients who are at an increased risk for decreased BMD that the use of corticosteroids may pose an additional risk and should be monitored and, where appropriate, be treated for this condition [see Warnings and Precautions (5.9)].

Reduced Growth Velocity

Inform patients that orally inhaled corticosteroids, including ASMANEX HFA, may cause a reduction in growth velocity when administered to pediatric patients. Physicians should closely follow the growth of pediatric patients taking corticosteroids by any route [see Warnings and Precautions (5.10)].

Glaucoma and Cataracts

Advise patients that long-term use of inhaled corticosteroids may increase the risk of some eye problems (glaucoma or cataracts); consider regular eye examinations [see Warnings and Precautions (5.11)].

Hypersensitivity Reactions Including Anaphylaxis

Advise patients that hypersensitivity reactions, such as urticaria, flushing, allergic dermatitis, bronchospasm, rash, pruritus, angioedema, and anaphylactic reaction, may occur after administration of ASMANEX HFA. Instruct patients to discontinue ASMANEX HFA if such reactions occur [see Warnings and Precautions (5.8)].

Use Daily for Best Effect

Advise patients to use ASMANEX HFA at regular intervals, since its effectiveness depends on regular use. Maximum benefit may not be achieved for 1 week or longer after starting treatment. If symptoms do not improve after 2 weeks of therapy or if the condition worsens, instruct patients to contact their physician.

Instructions for Use

Instruct patients regarding the following:

- Read the Patient Information before use and follow the Instructions for Use carefully.
- Remind patients to:
  - Remove the cap from the mouthpiece of the actuator before use.
  - After dosing, rinse their mouth with water and spit out contents without swallowing. This will help reduce the risk of oropharyngeal candidiasis.
  - Not remove the canister from the actuator.
  - Not wash inhaler in water. The mouthpiece should be cleaned using a dry wipe after every 7 days of use.

Manufactured for: Organon LLC, a subsidiary of
ORGANON & Co.,
Jersey City, NJ 07302, USA

Manufactured by: Kindeva Drug Delivery Limited, Loughborough, United Kingdom.

For patent information: www.organon.com/our-solutions/patent/

© 2025 Organon group of companies. All rights reserved.

uspi-og0887-ao-2506r001

Patient Information
ASMANEX® HFA (AZ-ma-neks) 50 mcg
ASMANEX® HFA 100 mcg
ASMANEX® HFA 200 mcg
(mometasone furoate)
Inhalation Aerosol

What is ASMANEX HFA?
ASMANEX HFA is an inhaled corticosteroid (ICS) prescription medicine used as maintenance treatment for the prevention and control of asthma symptoms in people 5 years of age and older.

- ASMANEX HFA is not used to treat sudden severe symptoms of asthma.
- ASMANEX HFA should not be used as a rescue inhaler.
- It is not known if ASMANEX HFA is safe and effective in children less than 5 years of age.

Who should not use ASMANEX HFA?
Do not use ASMANEX HFA:

- to treat sudden severe symptoms of asthma.
- if you are allergic to mometasone furoate or any of the ingredients in ASMANEX HFA. See the end of this Patient Information leaflet for a complete list of ingredients in ASMANEX HFA.

What should I tell my doctor before and during treatment with ASMANEX HFA?
Before you use ASMANEX HFA, tell your healthcare provider if you:

- have liver problems.
- have osteoporosis.
- have an immune system problem.
- have eye problems such as increased pressure in the eye, glaucoma, cataracts, blurred vision, or other changes in your vision.
- are allergic to any medicines.
- are exposed to chickenpox or measles.
- have or had tuberculosis (TB).
- have any other medical problems.
- are pregnant or planning to become pregnant. It is not known if ASMANEX HFA may harm your unborn baby.
- are breastfeeding. It is not known if ASMANEX HFA passes into your breast milk and if it can harm your baby. You and your healthcare provider should decide if you will either take ASMANEX HFA or breastfeed.

Tell your healthcare provider about all the medicines you take, including prescription and over-the-counter medicines, vitamins, and herbal supplements.
ASMANEX HFA may affect the way other medicines work, and other medicines may affect how ASMANEX HFA works.
Especially, tell your healthcare provider if you take antifungal medicines, antibiotic medicines, or anti-HIV medicines such as:

- ritonavir
- atazanavir
- cobicistat-containing products

- ketoconazole
- clarithromycin

- nefazodone
- saquinavir

- nelfinavir
- telithromycin

- indinavir
- itraconazole

Ask your healthcare provider if you are not sure if any of your medicines are the kinds listed above.
For some medicines (including medicines for HIV such as ritonavir, cobicistat-containing products, and certain antifungals and antibiotics) your doctor may wish to monitor you carefully.
Know the medicines you take. Keep a list and show it to your healthcare provider and pharmacist each time you get a new medicine.

How should I use ASMANEX HFA?
Read the step-by-step instructions for using ASMANEX HFA in the Instructions for Use.

- Use ASMANEX HFA exactly as prescribed. Do not use ASMANEX HFA more often than prescribed.
- You must use ASMANEX HFA regularly. It may take 1 week or longer after you start using ASMANEX HFA for your asthma symptoms to get better. Do not stop using ASMANEX HFA even if you are feeling better, unless your healthcare provider tells you to.
- Do not change or stop using ASMANEX HFA or other asthma medicines used to control or treat your breathing problems unless told to do so by your healthcare provider. Your healthcare provider will change your medicines as needed.
- ASMANEX HFA comes in 3 strengths. Your healthcare provider has prescribed the strength that is best for you. Pay attention to the differences between ASMANEX HFA and your other inhaled medicines, including their prescribed use and the way they look.
- For children aged 5 to less than 12 years, use ASMANEX HFA 50 mcg.
- For adults and adolescents 12 years of age and older, use ASMANEX HFA 100 mcg or 200 mcg.
- Take ASMANEX HFA every day, with 2 puffs in the morning and 2 puffs in the evening.
- If you miss a dose of ASMANEX HFA, skip your missed dose and take your next dose at your regular time. Do not take ASMANEX HFA more often or use more puffs than you have been prescribed.
- If you take more ASMANEX HFA than your healthcare provider has prescribed, call your healthcare provider right away.
- ASMANEX HFA does not relieve sudden asthma symptoms. Always have a rescue inhaler with you to treat sudden symptoms. Use your rescue inhaler if you have breathing problems between doses of ASMANEX HFA. If you do not have a rescue inhaler, call your healthcare provider to have a rescue inhaler prescribed for you.
- Do not use the ASMANEX HFA canister or actuator with any other medicines. Do not use any other medicine canister or actuator with ASMANEX HFA.
- Rinse your mouth with water after each dose (2 puffs) of ASMANEX HFA. Spit out the water. Do not swallow it. This will help to lessen the chance of getting a yeast infection (thrush) in your mouth and throat.
- Do not spray ASMANEX HFA in your eyes. If you accidentally get ASMANEX HFA in your eyes, rinse your eyes with water and if redness or irritation continues, call your healthcare provider.
- Call your healthcare provider or get medical care right away if:
  - your breathing problems worsen with ASMANEX HFA
  - you need to use your rescue inhaler more often than usual
  - your rescue inhaler does not work as well for you at relieving symptoms
  - you need to use 4 or more inhalations of your rescue inhaler for 2 or more days in a row
  - you use 1 whole canister of your rescue inhaler within 8 weeks
  - your peak flow meter results decrease. Your healthcare provider will tell you the numbers that are right for you
  - you have asthma and your symptoms do not improve after using ASMANEX HFA regularly for 1 to 2 weeks

What are the possible side effects of ASMANEX HFA?
ASMANEX HFA can cause serious side effects, including

- Thrush in your mouth and throat. You may develop thrush, a yeast infection (Candida albicans), in your mouth or throat. After each dose (2 puffs) of ASMANEX HFA, rinse your mouth with water. Spit out the water. Do not swallow it. This will help to prevent thrush in your mouth or throat.
- Immune system effects and a higher chance for infections.
  Tell your healthcare provider about any signs of infection such as:

- fever

- feeling tired

- body aches

- vomiting

- pain

- nausea

- chills

- Adrenal insufficiency that can lead to death can happen when you stop taking oral corticosteroid medicines and start using inhaled corticosteroid medicines. Adrenal insufficiency can also happen in people who take higher doses of ASMANEX HFA than recommended over a long period of time. When your body is under stress such as from fever, trauma (such as a car accident), infection, or surgery, adrenal insufficiency can get worse. Symptoms of adrenal insufficiency include:

- feeling tired or exhausted (fatigue)
- weakness

- lack of energy
- nausea and vomiting

- low blood pressure (hypotension)
- dizziness or feeling faint

- Increased wheezing right after taking ASMANEX HFA. Always have a rescue inhaler with you to treat sudden wheezing.
- Serious allergic reactions. Stop taking ASMANEX HFA and call your healthcare provider or get emergency medical care right away if you get any of the following symptoms of a serious allergic reaction:

- rash

- hives

- swelling, including swelling of the face, mouth, and tongue

- breathing problems

- Lower bone mineral density. This may be a problem for people who already have a higher chance for low bone density (osteoporosis).
- Slowed growth in children. A child's growth should be checked often.
- Eye problems including glaucoma, cataracts, and blurred vision. You should have regular eye exams while using ASMANEX HFA.

The most common side effects reported while using ASMANEX HFA include:

- inflammation of the nose and throat (nasopharyngitis)
- inflammation of the sinuses (sinusitis)

- headache
- bronchitis

- flu infection (influenza)

Other side effects: Worsening asthma or sudden asthma attacks have been reported with the use of inhaled mometasone furoate.
Tell your healthcare provider about any side effect that bothers you or that does not go away.
These are not all the side effects with ASMANEX HFA. Ask your healthcare provider or pharmacist for more information.
Call your doctor for medical advice about side effects. You may report side effects to FDA at 1-800-FDA-1088.

How should I store ASMANEX HFA?

- Store ASMANEX HFA at room temperature between 68°F to 77°F (20°C to 25°C).
- After priming, store the inhaler with the mouthpiece down or sideways.
- The contents of your ASMANEX HFA are under pressure. Do not puncture. Do not use or store near heat or open flame. Storage above 120°F may cause the canister to burst.
- Do not throw container into fire or incinerator.
- Keep ASMANEX HFA and all medicines out of the reach of children.

General Information about the safe and effective use of ASMANEX HFA.
Medicines are sometimes prescribed for purposes other than those listed in a Patient Information leaflet. Do not use ASMANEX HFA for a condition for which it was not prescribed. Do not give your ASMANEX HFA to other people, even if they have the same condition that you have. It may harm them.
This Patient Information leaflet summarizes the most important information about ASMANEX HFA. If you would like more information, talk with your healthcare provider. You can ask your healthcare provider or pharmacist for information about ASMANEX HFA that was written for healthcare professionals.
For more information about ASMANEX HFA go to www.ASMANEX.com, or to report side effects call 1-844-674-3200.

What are the ingredients in ASMANEX HFA?
Active ingredient: mometasone furoate
Inactive ingredients: hydrofluoroalkane (HFA-227: 1,1,1,2,3,3,3-heptafluoropropane), ethanol and oleic acid

This Patient Information has been approved by the U.S. Food and Drug Administration.

Revised Date: 6/2025

Instructions for Use

ASMANEX® HFA (AZ-ma-neks) 50 mcg
ASMANEX® HFA 100 mcg
ASMANEX® HFA 200 mcg
(mometasone furoate)
Inhalation Aerosol

Read these Instructions for Use before you start using ASMANEX HFA and each time you get a refill. There may be new information. This leaflet does not take the place of talking to your healthcare provider about your medical condition or your treatment.

The parts of your ASMANEX HFA:

There are 2 main parts to your ASMANEX HFA inhaler: the metal canister that holds the medicine and the blue plastic actuator that sprays the medicine from the canister.

- The inhaler also has a pink cap that covers the mouthpiece of the actuator (see Figure 1). The cap from the mouthpiece must be removed before use. The inhaler contains "120" actuations (puffs).

Figure 1

- The inhaler comes with a dose counter located on the plastic actuator (see Figure 1). The counter display will show the number of actuations (puffs) of medicine remaining. The first time you use ASMANEX HFA the dose counter will show "124" actuations remaining. Each time you press the canister, a puff of medicine is released and the counter will count down by 1. The counter will stop counting at 0.

Important Information:

- Use ASMANEX HFA exactly as your healthcare provider tells you to. Adults may assist children with using ASMANEX HFA as prescribed. Children may use ASMANEX HFA with or without a spacer device.
- Remove the cap from the mouthpiece of the actuator before using ASMANEX HFA.
- Do not remove the canister from the actuator because:
  - you may not receive the correct amount of medication.
  - the dose counter may not function properly.
  - if you try to insert the canister back into the actuator this may cause the dose counter to count down by 1 and may discharge a puff.
- Use the ASMANEX HFA canister only with the actuator supplied with the product. Do not use parts of the ASMANEX HFA inhaler with parts from any other inhalation medicine.

Before using your ASMANEX HFA:

Remove the cap from the mouthpiece of the actuator before using ASMANEX HFA (see Figure 2). Check the mouthpiece for objects before use. Make sure the canister is fully inserted into the actuator.

Figure 2

Priming your ASMANEX HFA Inhaler:

Before you use ASMANEX HFA for the first time, you must prime the inhaler.

1. To prime the inhaler, hold it in the upright position away from your face, and press down firmly and fully on the top of the canister until it stops moving in the actuator. Do this 4 times to release a total of 4 actuations (puffs) into the air.
2. Shake the inhaler well before each of the priming actuations. After priming 4 times, the dose counter should read "120".
3. If you do not use your ASMANEX HFA for more than 5 days, you will need to prime it again before use.

Using your ASMANEX HFA:

4. Confirm that the strength indicated on the actuator and canister labels matches the prescribed dosage.
5. Remove the cap from the mouthpiece of the actuator (see Figure 3). Check the mouthpiece for objects before use. Make sure the canister is fully inserted into the actuator.
6. Shake the inhaler well before each use.
7. Breathe out as fully as you comfortably can through your mouth. Push out as much air from your lungs as possible. Hold the inhaler in the upright position and place the mouthpiece into your mouth (see Figure 4). Close your lips around the mouthpiece.

Figure 3

Figure 4

8. Take a deep breath (inhale) in slowly through your mouth. While doing this, press down firmly and fully on the top of the canister until it stops moving in the actuator. Take your finger off the canister.
9. When you have finished breathing in, hold your breath as long as you comfortably can, up to 10 seconds. Then remove the inhaler from your mouth and breathe out through your nose, while keeping your lips closed.
10. Wait at least 30 seconds to take your second puff of ASMANEX HFA.
11. Shake the inhaler well again and repeat steps 6 through 8 to take your second puff of ASMANEX HFA.

After using your ASMANEX HFA inhaler:

12. Replace the cap over the mouthpiece right away after use (see Figure 5).

Figure 5

13. After you finish taking ASMANEX HFA (2 puffs), rinse your mouth with water.

Reading the counter:

- The dose counter identifies the number of inhalations (puffs) left in your inhaler (see Figure 6).
- The counter will count down each time you release a puff of medicine (either when preparing your ASMANEX HFA inhaler for use or when using the medicine).

Figure 6

When to replace your ASMANEX HFA:

- It is important that you pay attention to the number of inhalations (puffs) left in your ASMANEX HFA inhaler by reading the counter.
- When the counter reads "20", you should refill your prescription or ask your healthcare provider if you need a new prescription for ASMANEX HFA.
- Throw away ASMANEX HFA after the counter reaches "0", indicating that you have used the number of actuations on the product label and box. Your inhaler may not feel empty and it may continue to operate, but you will not get the right amount of medicine if you keep using it.
- Never try to change the numbers on the counter or remove the counter from the actuator.
- Do not use the inhaler after the expiration date.

How to clean your ASMANEX HFA:

The mouthpiece should be cleaned using a dry wipe after every 7 days of use.

Routine cleaning instructions:

- Remove the cap off the mouthpiece. Wipe the inside and outside surfaces of the actuator mouthpiece with a clean, dry, lint-free tissue or cloth. Do not wash or put any parts of your inhaler in water. Put the cap back on the mouthpiece after cleaning.
- Do not remove the canister from the actuator.
- Do not attempt to unblock the actuator with a sharp object, such as a pin.

This Instructions for Use has been approved by the U.S. Food and Drug Administration.

Manufactured for: Organon LLC, a subsidiary of
ORGANON & Co.,
Jersey City, NJ 07302, USA

Manufactured by: Kindeva Drug Delivery Limited, Loughborough, United Kingdom.
For patent information: www.organon.com/our-solutions/patent/
The trademarks depicted herein are owned by their respective companies.
© 2025 Organon group of companies. All rights reserved.

Revised: 6/2025
usppi-og0887-ao-2506r001

PRINCIPAL DISPLAY PANEL - 100 mcg Canister Carton

NDC 78206-112-01

Asmanex® HFA
(mometasone furoate)
Inhalation Aerosol

100 mcg per actuation

For oral inhalation only

Asmanex HFA canister to be used
with Asmanex HFA actuator only.

SHAKE WELL BEFORE USING.

Rx only

120 Metered Actuations
Net Wt. 13g

PRINCIPAL DISPLAY PANEL - 200 mcg Canister Carton

NDC 78206-113-01

Asmanex® HFA
(mometasone furoate)
Inhalation Aerosol

200 mcg per actuation

For oral inhalation only

Asmanex HFA canister to be used
with Asmanex HFA actuator only.

SHAKE WELL BEFORE USING.

Rx only

120 Metered Actuations
Net Wt. 13g

PRINCIPAL DISPLAY PANEL - 50 mcg Canister Carton

NDC 78206-111-01

Asmanex® HFA
(mometasone furoate)
Inhalation Aerosol

50 mcg per actuation

For oral inhalation only

Asmanex HFA canister to be used
with Asmanex HFA actuator only.

SHAKE WELL BEFORE USING.

Rx only

120 Metered Actuations
Net Wt. 13g